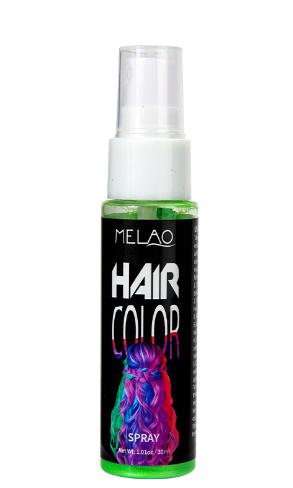 DRUG LABEL: MELAO HAIR COLOR PRODUCTS
NDC: 83566-580 | Form: SPRAY
Manufacturer: Guangzhou Yilong Cosmetics Co., Ltd
Category: otc | Type: HUMAN OTC DRUG LABEL
Date: 20240815

ACTIVE INGREDIENTS: .ALPHA.,.ALPHA.-DIMETHYLBENZYL ALCOHOL 3 g/100 g; LINALOOL, (+)- 1 g/100 g
INACTIVE INGREDIENTS: BENZYL BENZOATE 0.9 g/100 g; ISOMETHYL-.BETA.-IONONE, (E)- 0.1 g/100 g; GERANIOL 2.4 g/100 g; AQUA REGIA 59 g/100 g; ACRYLATES CROSSPOLYMER-6 7 g/100 g; CARBOXYPOLYMETHYLENE 4 g/100 g; BENZYL CINNAMATE 2.3 g/100 g; BUTYLPHENYL METHYLPROPIONAL 2 g/100 g; BENZYL SALICYLATE 3 g/100 g; ALCOHOL 8 g/100 g; PARFUMIDINE 4 g/100 g; CINNAMYL ALCOHOL 3.7 g/100 g

30ml HAIR COLOR SPRAY

Active ingredients

Benzyl Alcohol 3%

Linalool 1%

Inactive ingredients

Aqua 59%

Alcohol Denat 8%

Acrylates/VA Copolymer 7%

Polymethyl Methacrylate 4%

Parfum 4%

Cinnamyl Alcohol 3.70%

Benzyl Salicylate 3.00%

Geraniol 2.40%

Benzyl Cinnamate 2.30%

Butylphenyl Methylpropional 2

Benzyl Benzoate 0.90%

Alpha-Isomethyl Ionone 0.10%

Purpose

Disposable hair dye

Uses

Step 1: Clean and thoroughly dry your hair.
Step 2: Press and spray paint at a distance of 5 to 10cm from the hair.
Step3: Then comb your hair open and dry it.

Warning

For external use only.

Stop use and ask a doctor if

rash occurs.

Do not use

on damaged or broken skin.

When using this product

keep out of eyes. Rinse withwater to remove.

Keep out of reach of children.

If swallowed, get medical help or contact a Poison Control Center right away.

DOSAGE & ADMINISTRATION

Squeeze out an appropriate amount of sunscreen and spread evenly on skin.